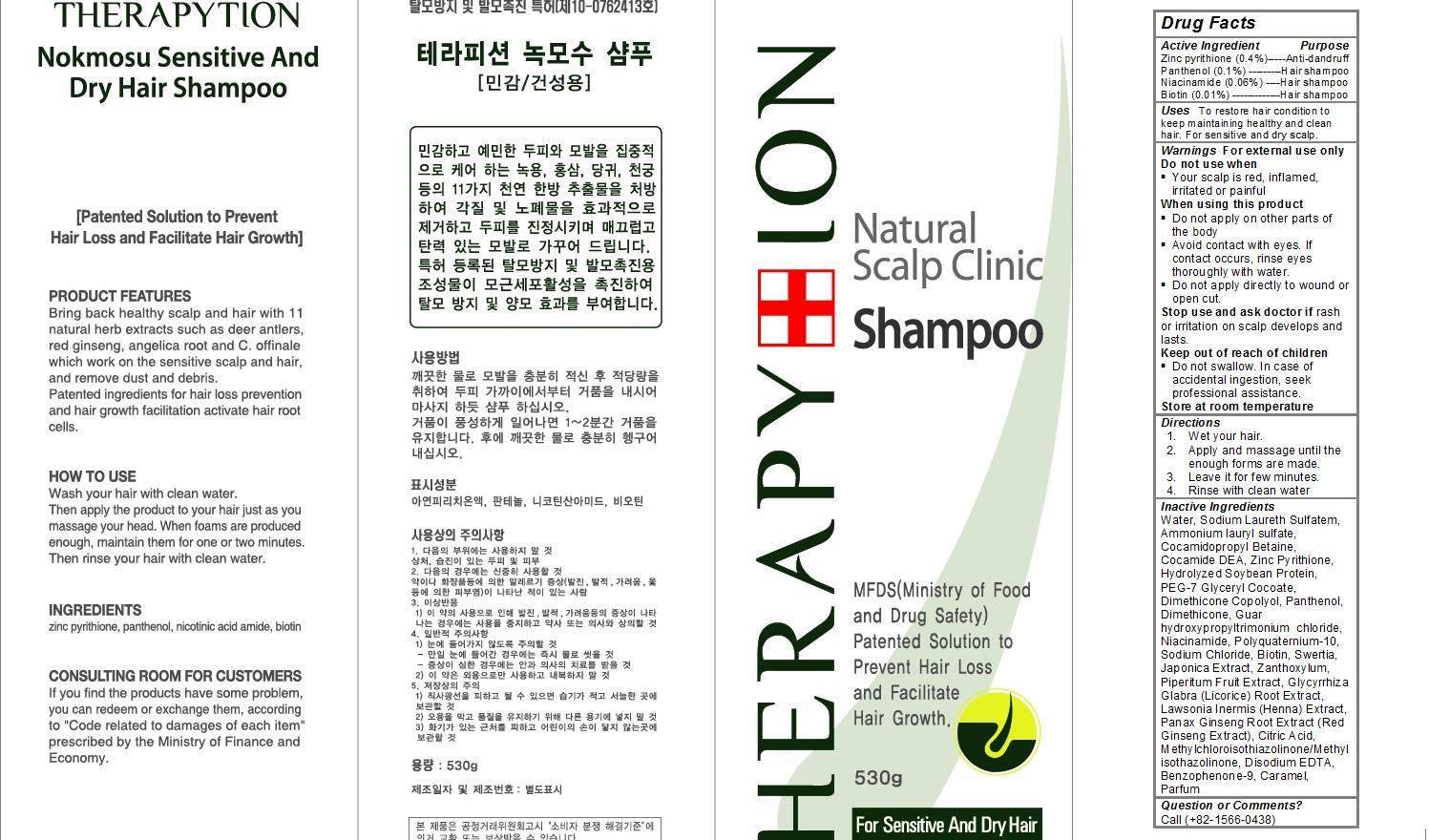 DRUG LABEL: Therapytion Nokmosu Sensitive and Dry Hair
NDC: 63214-101 | Form: SHAMPOO
Manufacturer: Therapytion Co., Ltd.
Category: otc | Type: HUMAN OTC DRUG LABEL
Date: 20140428

ACTIVE INGREDIENTS: PYRITHIONE ZINC 2.1 g/530 g; PANTHENOL 0.5 g/530 g; NIACINAMIDE 0.3 g/530 g; BIOTIN 0.06 g/530 g
INACTIVE INGREDIENTS: Water; Sodium Laureth Sulfate; Ammonium lauryl sulfate; Cocamidopropyl Betaine; PEG-6 COCAMIDE; SOYBEAN; PEG-7 Glyceryl Cocoate; DIMETHICONE; Sodium Chloride; SWERTIA JAPONICA; GLYCYRRHIZA GLABRA WHOLE; PANAX GINSENG ROOT OIL; CITRIC ACID ACETATE; DISODIUM EDTA-COPPER; Benzophenone-9; Caramel

Therapytion Nokmosu Sensitive and Dry Hair shampoo